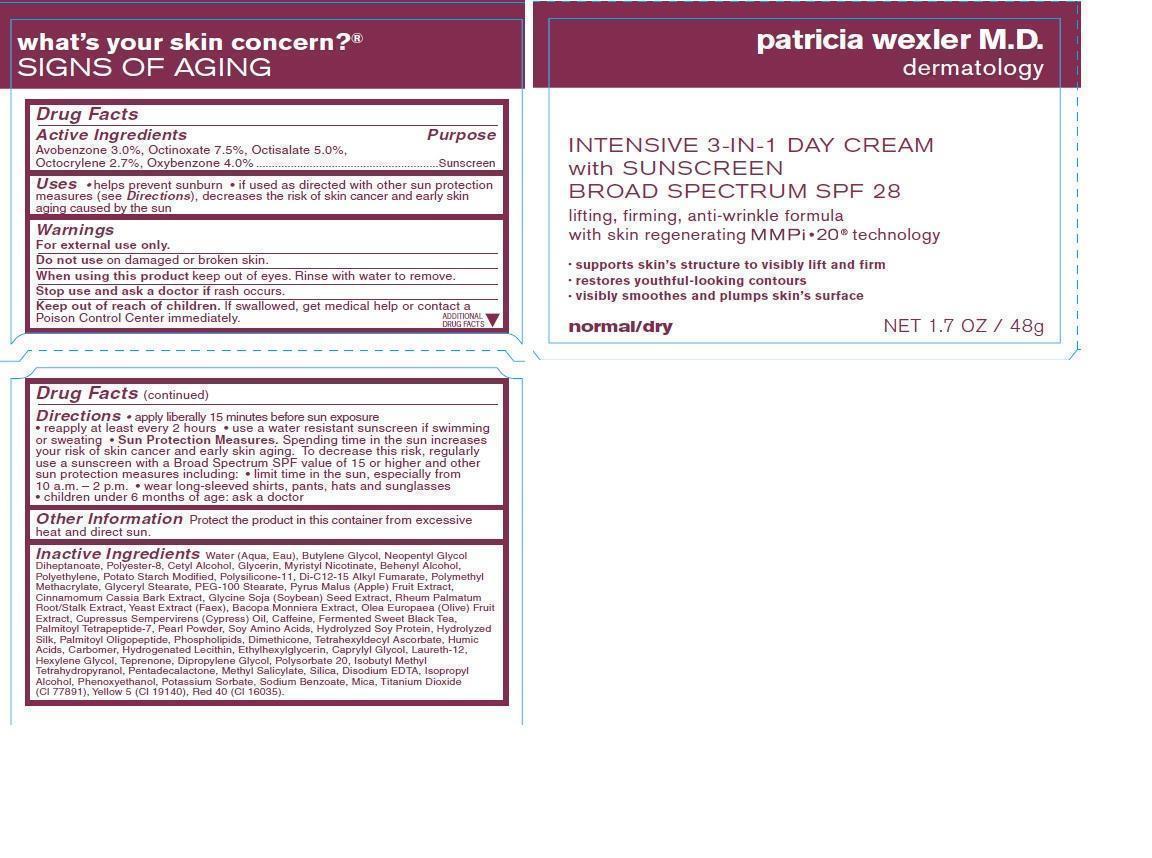 DRUG LABEL: Patricia Wexler Intensive 3-in-1 Day Cream with Sunscreen Broad Spectrum SPF 28
NDC: 62670-8047 | Form: CREAM
Manufacturer: Bath & Body Works, Inc.
Category: otc | Type: HUMAN OTC DRUG LABEL
Date: 20130930

ACTIVE INGREDIENTS: AVOBENZONE 3.0 mg/1 g; OCTINOXATE 7.5 mg/1 g; OCTISALATE 5.0 mg/1 g; OCTOCRYLENE 2.7 mg/1 g; OXYBENZONE 4.0 mg/1 g
INACTIVE INGREDIENTS: WATER

ACTIVE INGREDIENT

Avobenzone 3.0%, Octinoxate 7.5%, Octisalate 5.0%, Octocrylene 2.7%, Oxybenzone 4.0%

PURPOSE

Sunscreen

USES

- helps prevent sunburn
- if used as directed with other sun protection measures (see Directions), decreases the risk of skin cancer and early skin aging caused by the sun

WARNINGS

For external use only.

DO NOT USE

on damaged or broken skin.

WHEN USING THIS PRODUCT

keep out of eyes. Rinse with water to remove.

STOP USE AND ASK A DOCTOR IF

rash occurs.

KEEP OUT OF REACH OF CHILDREN.

If swallowed, get medical help or contact a Poison Control Center immediately.

DIRECTIONS

- apply liberally 15 minutes before sun exposure
- reapply at least every 2 hours
- use a water resistant sunscreen if swimming or sweating
- Sun Protection Measures. Spending time in the sun increases your risk of skin cancer and early skin aging. To decrease this risk, regularly use a sunscreen with a Broad Spectrum SPF value of 15 or higher and other sun protection measures including:
- limit time in the sun, especially from 10 a.m. - 2 p.m.
- wear long-sleeved shirts, pants, hats and sunglasses
- children under 6 months of age: ask a doctor

OTHER INFORMATION

Protect the product in this container from excessive heat and direct sun.

INACTIVE INGREDIENTS

Water (Aqua, Eau), Butylene Glycol, Neopentyl Glycol Diheptanoate, Polyester-8, Cetyl Alcohol, Glycerin, Myristyl Nicotinate, Behenyl Alcohol, Polyethylene, Potato Starch Modified, Polysilicone-11, Di-C12-15 Alkyl Fumarate, Polymethyl Methacrylate, Glyceryl Stearate, PEG-100 Stearate, Pyrus Malus (Apple) Fruit Extract, Cinnamomum Cassia Bark Extract, Glycine Soja (Soybean) Seed Extract, Rheum Palmatum Root/Stalk Extract, Yeast Extract (Faex), Bacopa Monniera Extract, Olea Europaea (Olive) Fruit Extract, Cupressus Sempervirens (Cypress) Oil, Caffeine, Fermented Sweet Black Tea, Palmitoyl Tetrapeptide-7, Pearl Powder, Soy Amino Acids, Hydrolyzed Soy Protein, Hydrolyzed Silk, Palmitoyl Oligopeptide, Phospholipids, Dimethicone, Tetrahexyldecyl Ascorbate, Humic Acids, Carbomer, Hydrogenated Lecithin, Ethylhexylglycerin, Caprylyl Glycol, Laureth-12, Hexylene Glycol, Teprenone, Dipropylene Glycol, Polysorbate 20, Isobutyl Methyl Tetrahydropyranol, Pentadecalactone, Methyl Salicylate, Silica, Disodium EDTA, Isopropyl Alcohol, Phenoxyethanol, Potassium Sorbate, Sodium Benzoate, Mica, Titanium Dioxide (CI 77891), Yellow 5 (CI 19140), Red 40 (CI 16035).

COMPANY INFORMATION

Bath & Body Works, Distr.

Reynoldsburg, Ohio 43068

1-800-395-1001

www.bathandbodyworks.com